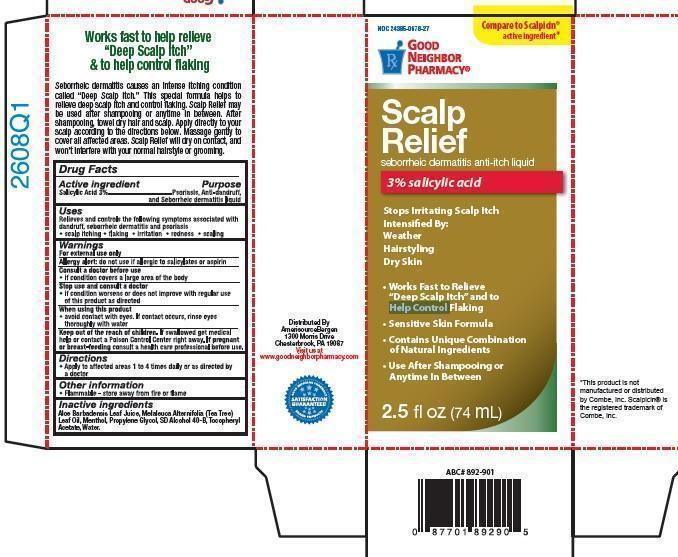 DRUG LABEL: Good Neighbor Pharmacy Scalp Relief
NDC: 24385-678 | Form: LIQUID
Manufacturer: AmerisourceBergen Drug Corportaion
Category: otc | Type: HUMAN OTC DRUG LABEL
Date: 20150722

ACTIVE INGREDIENTS: SALICYLIC ACID 3 g/100 g
INACTIVE INGREDIENTS: ALOE VERA LEAF  ; MELALEUCA ALTERNIFOLIA LEAF; MENTHOL; PROPYLENE GLYCOL; ALCOHOL; .ALPHA.-TOCOPHEROL ACETATE; WATER

Good Neighbor Pharmacy Scalp Relief

Works fast to help relieve “Deep Scalp Itch” & to help control flaking Seborrheic dermatitis causes an intense itching condition called “Deep Scalp Itch.” This special formula helps to relieve deep scalp itch and control flaking. Scalp Relief may be used after shampooing or anytime in between. After shampooing, towel dry hair and scalp. Apply directly to your scalp according to the directions below. Massage gently to cover all affected areas. Scalp Relief will dry on contact, and won’t interfere with your normal hairstyle or grooming.

Drug Facts

Active ingredient

Salicylic Acid 3%

Purpose

Psoriasis, Anti-dandruff, and Seborrheic dermatitis liquid

Uses

Relieves and controls the following symptoms associated with

dandruff, seborrheic dermatitis and psoriasis

• scalp itching • flaking • irritation • redness • scaling

Warnings

For external use only

Consult a doctor before use

• if condition covers a large area of the body

Stop use and consult a doctor

• if condition worsens or does not improve with regular use

of this product as directed

When using this product

• avoid contact with eyes. If contact occurs, rinse eyes

thoroughly with water

Keep out of the reach of children.

If swallowed get medical help or contact a Poison Control Center right away.

If pregnant or breast-feeding consult a health care professional before use.

Directions

• Apply to affected areas 1 to 4 times daily or as directed by a doctor

Other information

• Flammable - store away from fire or flame

Inactive ingredients

Aloe Barbadensis Leaf Juice, Melaleuca Alternifolia (Tea Tree) Leaf Oil, Menthol, Propylene Glycol, SD Alcohol 40-B, Tocopheryl Acetate, Water.

Distributed By

AmerisourceBergen

1300 Morris Drive

Chesterbrook, PA 19087

Visit us at

www.goodneighborpharmacy.com